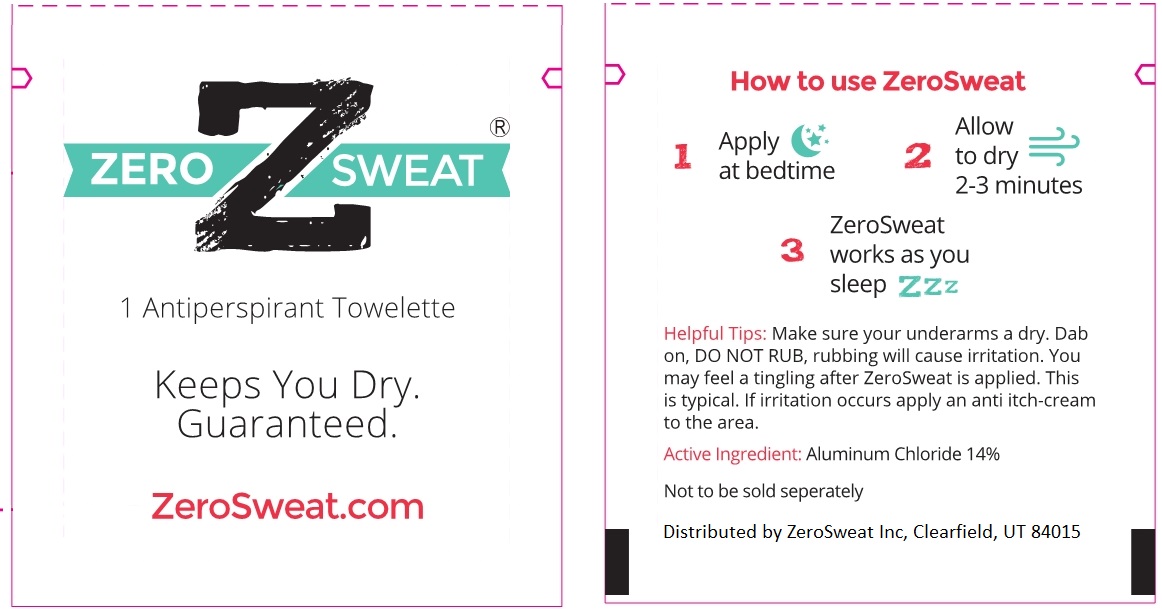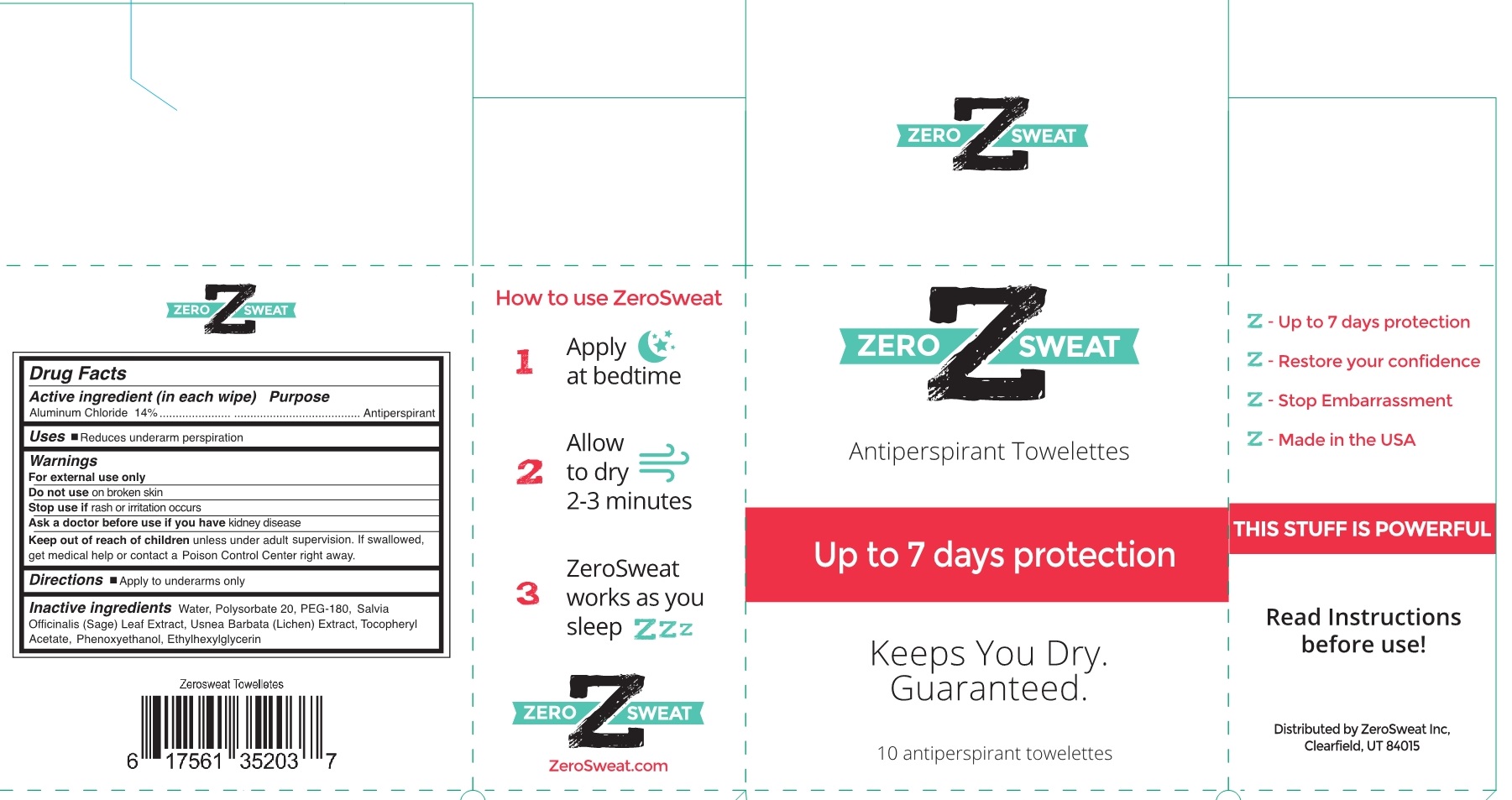 DRUG LABEL: Antiperspirant Towlette
NDC: 55726-200 | Form: CLOTH
Manufacturer: Zero Sweat
Category: otc | Type: HUMAN OTC DRUG LABEL
Date: 20190705

ACTIVE INGREDIENTS: ALUMINUM CHLORIDE 14 g/100 g
INACTIVE INGREDIENTS: WATER; POLYSORBATE 20; POLYETHYLENE GLYCOL 8000; SALVIA OFFICINALIS WHOLE; USNEA BARBATA; .ALPHA.-TOCOPHEROL ACETATE; PHENOXYETHANOL; ETHYLHEXYLGLYCERIN

Antiperspirant Towlette

Active Ingredient

Aluminum Chloride 14%

Purpose

Antiperspirant

Uses

Reduces underarm perspiration

Warnings

For external use only

Do not use on broken skin

Stop use if rash or irritation occurs

Ask a doctor before use if you have kidney disease

Keep out of reach of children unless under adult supervision. If swallowed get medical help or contact a Poison Control Center right away.

Directions

Apply to underarms only

Inactive ingredients

Water, Polysorbate 20, PEG-180, Salvia Officionalis (Sage) Leaf Extract, Usnea Barbata (Lichen) Extract, Tocopheryl Acetate, Phenoxyethanol, Ethylhexylglycerin